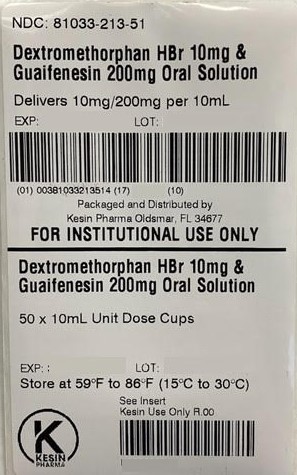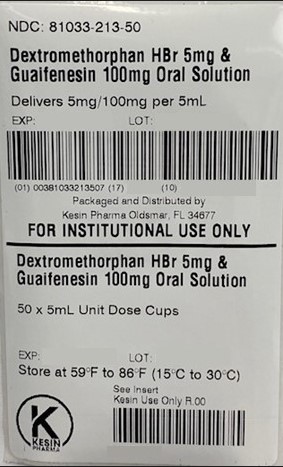 DRUG LABEL: Dextromethorphan HBr and Guaifenesin
NDC: 81033-213 | Form: LIQUID
Manufacturer: KESIN PHARMA CORPORATION
Category: otc | Type: HUMAN OTC DRUG LABEL
Date: 20231114

ACTIVE INGREDIENTS: DEXTROMETHORPHAN HYDROBROMIDE 5 mg/5 mL; GUAIFENESIN 100 mg/5 mL
INACTIVE INGREDIENTS: TRISODIUM CITRATE DIHYDRATE; ANHYDROUS CITRIC ACID; XANTHAN GUM; SODIUM BENZOATE; GLYCERIN; PROPYLENE GLYCOL; SUCRALOSE; SACCHARIN SODIUM; SORBITOL; WATER

Dextromethorphan HBr and Guaifenesin Oral Solution

Dextromethorphan HBr and Guaifenesin Oral Solution

DM Guaifenesin
Non-Narcotic, Sugar, Dye and Alcohol Free
Expectorant/Cough Suppressant

Active Ingredients – 5mL (1 teaspoonful) | Purposes
Guaifenesin 100 mg | Expectorant
Dextromethorphan 5 mg | Cough Suppressant

Inactive Ingredients

Trisodium citrate Dihydrate, Citric Acid Anhydrous, USP Xanthan Gum Sodium Benzoate, NF Glycerin 99.7%, USP Propylene Glycol Sucralose Powder Sodium Saccharin, USP Sorbitol Solution 70%, Non-Crystallizable Sodium Artificial Mixed Berry Flavor Purified Water

Uses

▪ Temporarily relieves cough due to minor throat and bronchial irritations as my occur with a cold
▪ Helps loosen phlegm (mucus) and thin bronchial secretions to drain bronchial tubes

Warnings

Do not use if you are now taking a prescription monoamine oxidase inhibitor (MAOI) (certain drugs for depression, psychiatric, or emotional conditions, or Parkinson’s disease), or for 2 weeks after stopping the MAOI drug. If you do not know if your prescription drug contains and MAOI, ask a doctor or pharmacist before taking this product.

Ask a doctor before use if you have

▪ Cough that occurs with too much phlegm (mucus)
▪ Cough that lasts or is chronic such as occurs with smoking, asthma, chronic bronchitis, or emphysema.

Stop use and ask a doctor if cough lasts more than 7 days, comes back, or is accompanied by fever, rash, or persistent headache. These could be signs of a serious condition.

PREGNANCY OR BREAST FEEDING

If pregnant or breast-feeding, ask a health professional before use.

Keep out of reach of children. In case of overdose, get medical help or contact a Poison Control Center right away.

Directions
▪ Do not take more than 6 doses in any 24-hour period

Age | Dose
adults and children 12 years and over | 10mL (2 teaspoonful) every 4 hours
children 6 to under 12 years of age | 5mL (1 teaspoonful) every 4 hours
children 2 to under 6 years of age | 2.5mL (1/2 teaspoonful) every 4 hours
children under 2 years | consult a doctor

Other information

- Each teaspoonful contains: sodium 4 mg
- Store at 20° - 25°C (68° - 77°F)
- Alcohol/sugar free
- Clear, mixed berry flavored solutions supplied in the following oral dosage forms: NDC 81033-213-05 (unit dose cups of 5mL) and NDC 81033-213-10 (unit dose cups of 10mL)

QUESTIONS OR COMMENTS
Call 1-833-537-4679

PRINCIPAL DISPLAY PANEL - 5 mL Unit Dose Cup Label

NDC 81033-213-50

Dextromethorphan HBr and Guaifenesin Oral Solution

Delivers 5mg/100mg per 5mL

FOR INSTITUTIONAL USE ONLY

50 X 5 mL Unit Dose Cups

Store at 59°F to 86°F (15°C to 30°C)

PRINCIPAL DISPLAY PANEL - 10 mL Unit Dose Cup Label

NDC 81033-213-51

Dextromethorphan HBr and Guaifenesin Oral Solution

Delivers 10mg/200mg per 10mL

FOR INSTITUTIONAL USE ONLY

50 X 10 mL Unit Dose Cups

Store at 59°F to 86°F (15°C to 30°C)